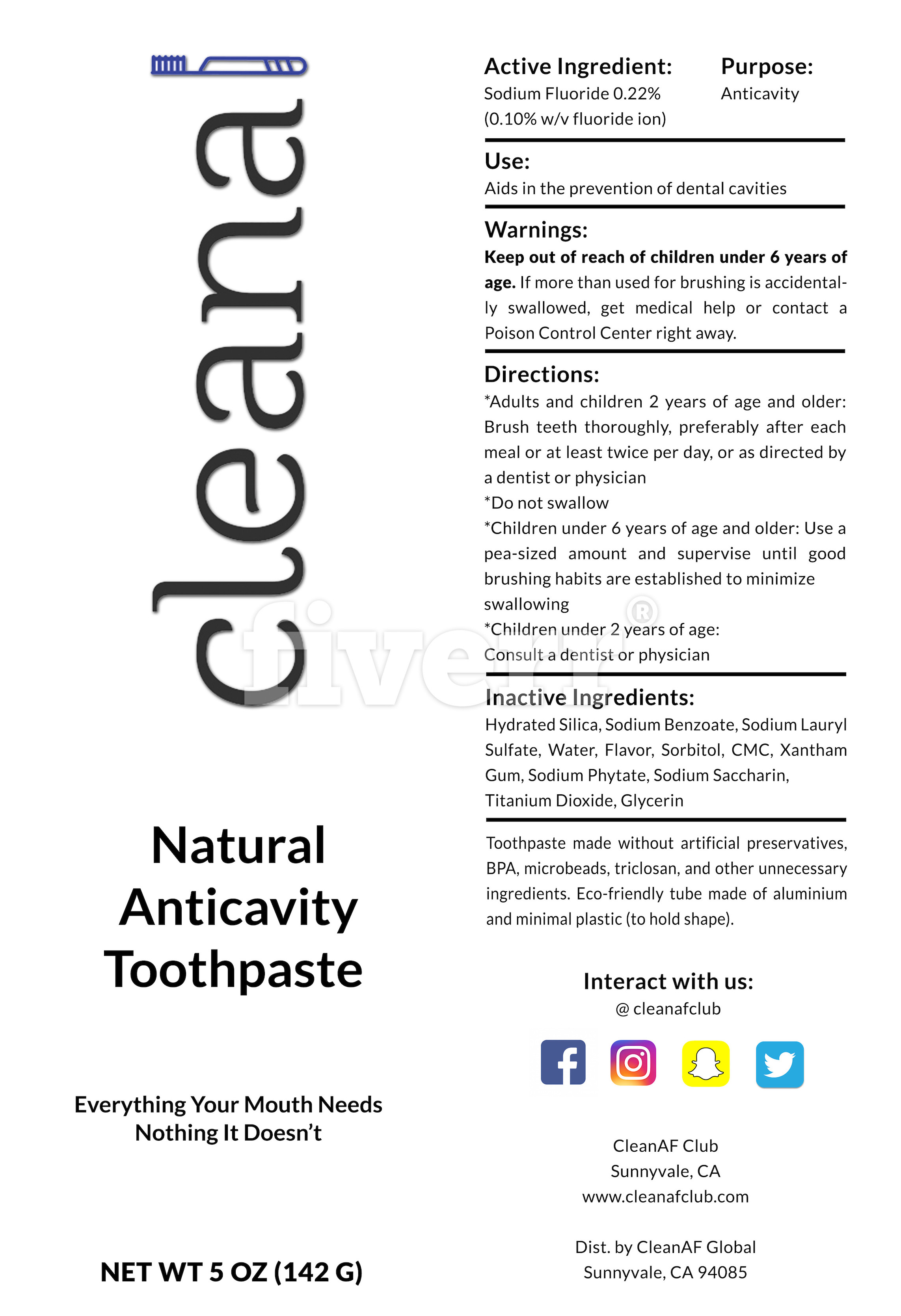 DRUG LABEL: CleanAFNaturalAnticavityToothpaste
NDC: 71603-1700 | Form: PASTE
Manufacturer: CLEANAF GLOBAL LIMITED LIABILITY COMPANY
Category: otc | Type: HUMAN OTC DRUG LABEL
Date: 20170714

ACTIVE INGREDIENTS: SODIUM FLUORIDE 0.22 g/100 g
INACTIVE INGREDIENTS: HYDRATED SILICA; SODIUM BENZOATE; SODIUM LAURYL SULFATE; WATER; TITANIUM DIOXIDE; GLYCERIN; CARBOXYMETHYLCELLULOSE SODIUM; SORBITOL; XANTHAN GUM; PHYTATE SODIUM; SACCHARIN SODIUM

CleanAF Toothpaste

PACKAGE LABEL

ACTIVE INGREDIENT

Sodium Fluoride 0.22% (0.10% w/v fluoride ion)

INACTIVE INGREDIENT

Hydrated Silica, sodium benzoate, sodium lauryl sulfate, water, flavor, sorbitol, CMC, xantham gum, sodium phytate, sodium saccharin, titanium dioxide, glycerin

PURPOSE

Anticavity

WARNINGS

Do not swallow